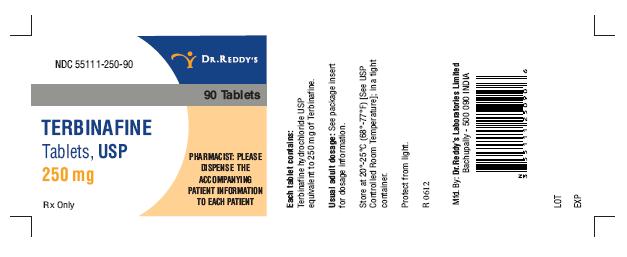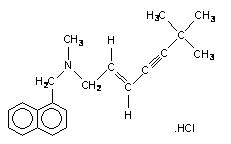 DRUG LABEL: Terbinafine Hydrochloride 
NDC: 55111-250 | Form: TABLET
Manufacturer: Dr.Reddys Laboratories Limited
Category: prescription | Type: HUMAN PRESCRIPTION DRUG LABEL
Date: 20241219

ACTIVE INGREDIENTS: TERBINAFINE HYDROCHLORIDE 250 mg/1 1
INACTIVE INGREDIENTS: SILICON DIOXIDE; CROSCARMELLOSE SODIUM; HYPROMELLOSES; magnesium stearate; CELLULOSE, MICROCRYSTALLINE

HIGHLIGHTS OF PRESCRIBING INFORMATION

These highlights do not include all the information needed to use terbinafine tablets safely and effectively. See full prescribing information for terbinafine tablets.
Terbinafine Tablets USP, 250 mg For oral use
Initial U.S. Approval: 1992

1 INDICATIONS AND USAGE

Terbinafine tablets are an allylamine antifungal indicated for the treatment of onychomycosis of the toenail or fingernail due to dermatophytes (tinea unguium)

2 DOSAGE AND ADMINISTRATION

- Fingernail onychomycosis: One 250 mg tablet, once daily for 6 weeks.
- Toenail onychomycosis: One 250 mg tablet, once daily for 12 weeks.

3 DOSAGE FORMS AND STRENGTHS

Tablet, 250 mg

4 CONTRAINDICATIONS

Terbinafine tablets are contraindicated in individuals with a history of allergic reaction to oral terbinafine because of the risk of anaphylaxis. (4)

5 WARNINGS AND PRECAUTIONS

- Liver failure, sometimes leading to liver transplant or death, has occurred with the use of oral terbinafine. Obtain pretreatment serum transaminases. Discontinue terbinafine tablets if liver injury develops. (5.1, 5.8)
- Taste disturbance, including taste loss, has been reported with the use of terbinafine tablets. Taste disturbance can be severe, may be prolonged, or may be permanent. Discontinue terbinafine tablets if taste disturbance occurs. (5.2)
- Smell disturbance, including loss of smell, has been reported with the use of terbinafine tablets. Smell disturbance may be prolonged, or may be permanent. Discontinue terbinafine tablets if smell disturbance occurs. (5.3)
- Depressive symptoms have been reported with terbinafine use. Prescribers should be alert to development of depressive symptoms. (5.4)
- Severe neutropenia has been reported. If the neutrophil count is ≤ 1,000 cells/mm^3, terbinafine tablets should be discontinued. (5.5)
- Stevens-Johnson syndrome and toxic epidermal necrolysis have been reported with oral terbinafine use. If progressive skin rash occurs, treatment with terbinafine tablets should be discontinued. (5.6)

6 ADVERSE REACTIONS

Common (>2% in patients treated with terbinafine tablets) reported adverse events include headache, diarrhea, rash, dyspepsia, liver enzyme abnormalities, pruritus, taste disturbance, nausea, abdominal pain, and flatulence. (6.1)

To report SUSPECTED ADVERSE REACTIONS, contact Dr. Reddy’s Laboratories, Inc. at 1-888-375-3784 or FDA at 1-800-FDA-1088 or www.fda.gov/medwatch.

7 DRUG INTERACTIONS

Terbinafine is an inhibitor of CYP4502D6 isozyme and has an effect on metabolism of desipramine, cimetidine, fluconazole, cyclosporine, rifampin, and caffeine. (7.1)

FULL PRESCRIBING INFORMATION

1 INDICATIONS AND USAGE

Terbinafine tablets are indicated for the treatment of onychomycosis of the toenail or fingernail due to dermatophytes (tinea unguium).

Prior to initiating treatment, appropriate nail specimens for laboratory testing (KOH preparation, fungal culture, or nail biopsy) should be obtained to confirm the diagnosis of onychomycosis.

2 DOSAGE AND ADMINISTRATION

Fingernail onychomycosis: One 250 mg tablet once daily for 6 weeks.

Toenail onychomycosis: One 250 mg tablet once daily for 12 weeks.

The optimal clinical effect is seen some months after mycological cure and cessation of treatment. This is related to the period required for outgrowth of healthy nail.

3 DOSAGE FORMS AND STRENGTHS

Tablet, 250 mg are white, round, flat, beveled edged tablets embossed ‘250’ on one side and ‘RDY’ on other side

4 CONTRAINDICATIONS

Terbinafine tablets are contraindicated in individuals with a history of allergic reaction to oral terbinafine because of the risk of anaphylaxis.

5 WARNINGS AND PRECAUTIONS

5.1 Hepatotoxicity

Cases of liver failure, some leading to liver transplant or death, have occurred with the use of terbinafine tablets in individuals with and without pre-existing liver disease.

In the majority of liver cases reported in association with terbinafine hydrochloride use, the patients had serious underlying systemic conditions. The severity of hepatic events and/or their outcome may be worse in patients with active or chronic liver disease. Treatment with terbinafine tablets should be discontinued if biochemical or clinical evidence of liver injury develops.

Terbinafine tablets are not recommended for patients with chronic or active liver disease. Before prescribing terbinafine tablets, pre-existing liver disease should be assessed. Hepatotoxicity may occur in patients with and without pre-existing liver disease. Patients prescribed terbinafine tablets should be warned to report immediately to their physician any symptoms of persistent nausea, anorexia, fatigue, vomiting, right upper abdominal pain or jaundice, dark urine or pale stools. Patients with these symptoms should discontinue taking oral terbinafine, and the patient’s liver function should be immediately evaluated.

5.2 Taste Disturbance Including Loss of Taste

Taste disturbance, including taste loss, has been reported with the use of terbinafine tablets. It can be severe enough to result in decreased food intake, weight loss, and depressive symptoms. Taste disturbance may resolve within several weeks after discontinuation of treatment, but may be prolonged (greater than one year), or may be permanent. If symptoms of a taste disturbance occur, terbinafine tablets should be discontinued.

5.3 Smell Disturbance Including Loss of Smell

Smell disturbance, including loss of smell, has been reported with the use of terbinafine tablets. Smell disturbance may resolve after discontinuation of treatment, but may be prolonged (greater than one year), or may be permanent. If symptoms of a smell disturbance occur, terbinafine tablets should be discontinued.

5.4 Depressive Symptoms

Depressive symptoms have occurred during postmarketing use of terbinafine. Prescribers should be alert to depressive symptoms, and patients should be instructed to report depressive symptoms to their physician.

5.5 Hematologic Effects

Transient decreases in absolute lymphocyte counts (ALC) have been observed in controlled clinical trials. In placebo-controlled trials, 8/465 terbinafine hydrochloride-treated patients (1.7%) and 3/137 placebo-treated patients (2.2%) had decreases in ALC to below 1000/mm^3 on two or more occasions. In patients with known or suspected immunodeficiency, physicians should consider monitoring complete blood counts if treatment continues for more than six weeks. Cases of severe neutropenia have been reported. These were reversible upon discontinuation of terbinafine hydrochloride, with or without supportive therapy. If clinical signs and symptoms suggestive of secondary infection occur, a complete blood count should be obtained. If the neutrophil count is <1,000 cells/mm^3, terbinafine hydrochloride should be discontinued and supportive management started.

5.6 Skin Reactions

There have been postmarketing reports of serious skin reactions (e.g., Stevens-Johnson Syndrome and toxic epidermal necrolysis). If progressive skin rash occurs, treatment with terbinafine tablets should be discontinued.

5.7 Lupus Erythematosus

During post-marketing experience, precipitation and exacerbation of cutaneous and systemic lupus erythematosus have been reported in patients taking terbinafine tablets. Terbinafine tablets should be discontinued in patients with clinical signs and symptoms suggestive of lupus erythematosus.

5.8 Laboratory Monitoring

Measurement of serum transaminases (ALT and AST) is advised for all patients before taking terbinafine tablets.

6 ADVERSE REACTIONS

6.1 Clinical Studies Experience

Because clinical trials are conducted under widely varying conditions, adverse reaction rates in the clinical trials of a drug cannot be directly compared to rates in the clinical trials of another drug and may not reflect the rates observed in practice. The most frequently reported adverse events observed in the three US/Canadian placebo-controlled trials are listed in the table below. The adverse events reported encompass gastrointestinal symptoms (including diarrhea, dyspepsia, and abdominal pain), liver test abnormalities, rashes, urticaria, pruritus, and taste disturbances. Changes in the ocular lens and retina have been reported following the use of terbinafine tablets in controlled trials. The clinical significance of these changes is unknown. In general, the adverse events were mild, transient, and did not lead to discontinuation from study participation.

 | Adverse Event |  | Discontinuation
 | Terbinafine tablet | Placebo | Terbinafine tablet | Placebo
 | (%) | (%) | (%) | (%)
 | n=465 | n=137 | n=465 | n=137
Headache | 12.9 | 9.5 | 0.2 | 0.0
Gastrointestinal
Symptoms:
Diarrhea | 5.6 | 2.9 | 0.6 | 0.0
Dyspepsia | 4.3 | 2.9 | 0.4 | 0.0
Abdominal Pain | 2.4 | 1.5 | 0.4 | 0.0
Nausea | 2.6 | 2.9 | 0.2 | 0.0
Flatulence | 2.2 | 2.2 | 0.0 | 0.0
Dermatological
Symptoms:
Rash | 5.6 | 2.2 | 0.9 | 0.7
Pruritus | 2.8 | 1.5 | 0.2 | 0.0
Urticaria | 1.1 | 0.0 | 0.0 | 0.0
Liver Enzyme
Abnormalities* | 3.3 | 1.4 | 0.2 | 0.0
Taste Disturbance | 2.8 | 0.7 | 0.2 | 0.0
Visual Disturbance | 1.1 | 1.5 | 0.9 | 0.0

* Liver enzyme abnormalities ≥ 2x the upper limit of normal range.

6.2 Postmarketing Experience

The following adverse events have been identified during post-approval use of terbinafine hydrochloride. Because these events are reported voluntarily from a population of uncertain size, it is not always possible to reliably estimate their frequency or establish a causal relationship to drug exposure.

Adverse events, based on worldwide experience with terbinafine tablets use, include: idiosyncratic and symptomatic hepatic injury and more rarely, cases of liver failure, some leading to death or liver transplant, serious skin reactions (e.g., Stevens-Johnson Syndrome and toxic epidermal necrolysis), severe neutropenia, thrombocytopenia, agranulocytosis, pancytopenia, anemia, angioedema, and allergic reactions (including anaphylaxis) [see Warnings and Precautions (5.1, 5.5 , and 5.6)].

Psoriasiform eruptions or exacerbation of psoriasis, acute generalized exanthematous pustulosis and precipitation and exacerbation of cutaneous and systemic lupus erythematosus have been reported in patients taking terbinafine hydrochloride [see Warnings and Precautions (5.7)].

Cases of taste disturbance, including taste loss, have been reported with the use of terbinafine tablets. It can be severe enough to result in decreased food intake, weight loss, and depressive symptoms [see Warnings and Precautions (5.2)]. Depressive symptoms independent of taste disturbance have been reported with use of terbinafine tablets. In some cases, depressive symptoms have been reported to subside with discontinuance of therapy and to recur with reinstitution of therapy [see Warnings and Precautions (5.4)]. Cases of smell disturbance, including smell loss, have been reported with the use of terbinafine tablets [see Warnings and Precautions (5.3)].

Other adverse reactions which have been reported include malaise, fatigue, vomiting, arthralgia, myalgia, rhabdomyolysis, reduced visual acuity, visual field defect, hair loss, serum sickness-like reaction, vasculitis, pancreatitis, influenza-like illness, pyrexia, increased blood creatine phosphokinase, photosensitivity reactions, tinnitus, hearing impairment and vertigo.

Altered prothrombin time (prolongation and reduction) in patients concomitantly treated with warfarin has been reported.

7 DRUG INTERACTIONS

7.1 Drug-Drug Interactions

In vivo studies have shown that terbinafine is an inhibitor of the CYP450 2D6 isozyme. Drugs predominantly metabolized by the CYP450 2D6 isozyme include the following drug classes: tricyclic antidepressants, selective serotonin reuptake inhibitors, beta-blockers, antiarrhythmics class 1C (e.g., flecainide and propafenone) and monoamine oxidase inhibitors Type B. Coadministration of terbinafine hydrochloride should be done with careful monitoring and may require a reduction in dose of the 2D6-metabolized drug. In a study to assess the effects of terbinafine on desipramine in healthy volunteers characterized as normal metabolizers, the administration of terbinafine resulted in a 2-fold increase in Cmax and a 5-fold increase in AUC. In this study, these effects were shown to persist at the last observation at 4 weeks after discontinuation of terbinafine tablets. In studies in healthy subjects characterized as extensive metabolizers of dextromethorphan (antitussive drug and CYP2D6 probe substrate), terbinafine increases the dextromethorphan/dextrorphan metabolite ratio in urine by 16- to 97-fold on average. Thus, terbinafine may convert extensive CYP2D6 metabolizers to poor metabolizer status.

In vitro studies with human liver microsomes showed that terbinafine does not inhibit the metabolism of tolbutamide, ethinylestradiol, ethoxycoumarin, cyclosporine, cisapride and fluvastatin. In vivo drug-drug interaction studies conducted in healthy volunteer subjects showed that terbinafine does not affect the clearance of antipyrine or digoxin. Terbinafine decreases the clearance of caffeine by 19%. Terbinafine increases the clearance of cyclosporine by 15%.

The influence of terbinafine on the pharmacokinetics of fluconazole, cotrimoxazole (trimethoprim and sulfamethoxazole), zidovudine or theophylline was not considered to be clinically significant.

Co-administration of a single dose of fluconazole (100mg) with a single dose of terbinafine resulted in a 52% and 69% increase in terbinafine Cmax and AUC, respectively. Fluconazole is an inhibitor of CYP2C9 and CYP3A enzymes. Based on this finding, it is likely that other inhibitors of both CYP2C9 and CYP3A4 (e.g., ketoconazole, amiodarone) may also lead to a substantial increase in the systemic exposure (Cmax and AUC) of terbinafine when concomitantly administered.

There have been spontaneous reports of increase or decrease in prothrombin times in patients concomitantly taking oral terbinafine and warfarin, however, a causal relationship between terbinafine tablets and these changes has not been established.

Terbinafine clearance is increased 100% by rifampin, a CYP450 enzyme inducer, and decreased 33% by cimetidine, a CYP450 enzyme inhibitor. Terbinafine clearance is unaffected by cyclosporine. There is no information available from adequate drug-drug interaction studies with the following classes of drugs: oral contraceptives, hormone replacement therapies, hypoglycemics, phenytoins, thiazide diuretics, and calcium channel blockers.

7.2 Food Interactions

An evaluation of the effect of food on terbinafine tablets was conducted. An increase of less than 20% of the AUC (i.e. area under the curve) of terbinafine was observed when terbinafine tablets were administered with food. Terbinafine tablets can be taken with or without food.

8 USE IN SPECIFIC POPULATIONS

8.1 Pregnancy

Pregnancy Category B: There are no adequate and well-controlled studies in pregnant women. Because animal reproduction studies are not always predictive of human response, and because treatment of onychomycosis can be postponed until after pregnancy is completed, it is recommended that terbinafine hydrochloride not be initiated during pregnancy.

Oral reproduction studies have been performed in rabbits and rats at doses up to 300 mg/kg/day (12x to 23x the MRHD, in rabbits and rats, respectively, based on BSA) and have revealed no evidence of impaired fertility or harm to the fetus due to terbinafine.

8.3 Nursing Mothers

After oral administration, terbinafine is present in breast milk of nursing mothers. The ratio of terbinafine in milk to plasma is 7:1. Treatment with terbinafine hydrochloride is not recommended in nursing mothers.

8.4 Pediatric Use

The safety and efficacy of terbinafine tablets have not been established in pediatric patients with onychomycosis.

8.5 Geriatric Use

Clinical studies of terbinafine tablets did not include sufficient numbers of subjects aged 65 and over to determine whether they respond differently from younger subjects. Other reported clinical experience has not identified differences in responses between the elderly and younger patients. In general, dose selection for an elderly patient should be cautious, usually starting at the low end of the dosing range, reflecting the greater frequency of decreased hepatic, renal, or cardiac function, and of concomitant disease or other drug therapy.

10 OVERDOSAGE

Clinical experience regarding overdose with oral terbinafine is limited. Doses up to 5 grams (20 times the therapeutic daily dose) have been taken without inducing serious adverse reactions. The symptoms of overdose included nausea, vomiting, abdominal pain, dizziness, rash, frequent urination, and headache.

11 DESCRIPTION

Terbinafine tablets contain the synthetic allylamine antifungal compound terbinafine hydrochloride. Chemically, terbinafine hydrochloride is (E)-N-(6,6-dimethyl-2-hepten-4-ynyl)-N-methyl-1-naphthalenemethanamine hydrochloride. The molecular formula C21H26CIN with a molecular weight of 327.90, and the following structural formula:

Terbinafine hydrochloride is a white to off-white fine crystalline powder. It is freely soluble in methanol and methylene chloride, soluble in ethanol, and slightly soluble in water.

Each tablet contains:

Active Ingredients: terbinafine hydrochloride (equivalent to 250 mg of terbinafine)

Inactive Ingredients: colloidal silicon dioxide, NF; croscarmellose sodium, NF; hypromellose, NF; magnesium stearate, NF; microcrystalline cellulose, NF.

12 CLINICAL PHARMACOLOGY

12.1 Mechanism of Action

Terbinafine is an allylamine antifungal [see Clinical Pharmacology (12.4)].

12.2 Pharmacodynamics

The pharmacodynamics of terbinafine hydrochloride is unknown.

12.3 Pharmacokinetics

Following oral administration, terbinafine is well absorbed (>70%) and the bioavailability of terbinafine tablets as a result of first-pass metabolism is approximately 40%. Peak plasma concentrations of 1 μg/mL appear within 2 hours after a single 250 mg dose; the AUC (area under the curve) is approximately 4.56 μg.h/mL. An increase in the AUC of terbinafine of less than 20% is observed when terbinafine tablets are administered with food.

In plasma, terbinafine is >99% bound to plasma proteins and there are no specific binding sites. At steady-state, in comparison to a single dose, the peak concentration of terbinafine is 25% higher and plasma AUC increases by a factor of 2.5; the increase in plasma AUC is consistent with an effective half-life of ~36 hours. Terbinafine is distributed to the sebum and skin. A terminal half-life of 200-400 hours may represent the slow elimination of terbinafine from tissues such as skin and adipose. Prior to excretion, terbinafine is extensively metabolized by at least seven CYP isoenzymes with major contributions from CYP2C9, CYP1A2, CYP3A4, CYP2C8 and CYP2C19. No metabolites have been identified that have antifungal activity similar to terbinafine. Approximately 70% of the administered dose is eliminated in the urine.

In patients with renal impairment (creatinine clearance <50 mL/min) or hepatic cirrhosis, the clearance of terbinafine is decreased by approximately 50% compared to normal volunteers. No effect of gender on the blood levels of terbinafine was detected in clinical trials. No clinically relevant age-dependent changes in steady-state plasma concentrations of terbinafine have been reported.

12.4 Microbiology

Terbinafine, an allylamine antifungal, inhibits biosynthesis of ergosterol, an essential component of fungal cell membrane, via inhibition of squalene epoxidase enzyme. This results in fungal cell death primarily due to the increased membrane permeability mediated by the accumulation of high concentrations of squalene but not due to ergosterol deficiency. Depending on the concentration of the drug and the fungal species test in vitro, terbinafine hydrochloride may be fungicidal. However, the clinical significance of in vitro data is unknown.

Terbinafine has been shown to be active against most strains of the following microorganisms both in vitro and in clinical infections:

Trichophyton mentagrophytes

Trichophyton rubrum

The following in vitro data are available, but their clinical significance is unknown. In vitro, terbinafine exhibits satisfactory MIC’s against most strains of the following microorganisms; however, the safety and efficacy of terbinafine in treating clinical infections due to these microorganisms have not been established in adequate and well-controlled clinical trials:

Candida albicans

Epidermophyton floccosum

Scopulariopsis brevicaulis

13 NONCLINICAL TOXICOLOGY

13.1 Carcinogenesis, Mutagenesis, Impairment Of Fertility

In a 28-month oral carcinogenicity study in rats, an increase in the incidence of liver tumors was observed in males at the highest dose tested, 69 mg/kg/day [2x the Maximum Recommended Human Dose (MRHD) based on AUC comparisons of the parent terbinafine]; however, even though dose-limiting toxicity was not achieved at the highest tested dose, higher doses were not tested.

The results of a variety of in vitro (mutations in E. coli and S. typhimurium, DNA repair in rat hepatocytes, mutagenicity in Chinese hamster fibroblasts, chromosome aberration and sister chromatid exchanges in Chinese hamster lung cells), and in vivo (chromosome aberration in Chinese hamsters, micronucleus test in mice) genotoxicity tests gave no evidence of a mutagenic or clastogenic potential.

Oral reproduction studies in rats at doses up to 300 mg/kg/day (approximately 12x the MRHD based on body surface area comparisons, BSA) did not reveal any specific effects on fertility or other reproductive parameters. Intravaginal application of terbinafine hydrochloride at 150 mg/day in pregnant rabbits did not increase the incidence of abortions or premature deliveries nor affect fetal parameters.

13.2 Animal Pharmacology and/or Toxicology

A wide range of in vivo studies in mice, rats, dogs, and monkeys, and in vitro studies using rat, monkey, and human hepatocytes suggest that peroxisome proliferation in the liver is a rat-specific finding. However, other effects, including increased liver weights and APTT, occurred in dogs and monkeys at doses giving Css trough levels of the parent terbinafine 2-3x those seen in humans at the MRHD. Higher doses were not tested.

14 CLINICAL STUDIES

The efficacy of terbinafine tablets in the treatment of onychomycosis is illustrated by the response of patients with toenail and/or fingernail infections who participated in three US/Canadian placebo-controlled clinical trials.

Results of the first toenail study, as assessed at week 48 (12 weeks of treatment with 36 weeks follow-up after completion of therapy), demonstrated mycological cure, defined as simultaneous occurrence of negative KOH plus negative culture, in 70% of patients. Fifty-nine percent (59%) of patients experienced effective treatment (mycological cure plus 0% nail involvement or >5mm of new unaffected nail growth); 38% of patients demonstrated mycological cure plus clinical cure (0% nail involvement).

In a second toenail study of dermatophytic onychomycosis, in which non-dermatophytes were also cultured, similar efficacy against the dermatophytes was demonstrated. The pathogenic role of the non-dermatophytes cultured in the presence of dermatophytic onychomycosis has not been established. The clinical significance of this association is unknown.

Results of the fingernail study, as assessed at week 24 (6 weeks of treatment with 18 weeks follow-up after completion of therapy), demonstrated mycological cure in 79% of patients, effective treatment in 75% of the patients, and mycological cure plus clinical cure in 59% of the patients.

The mean time to overall success was approximately 10 months for the first toenail study and 4 months for the fingernail study. In the first toenail study, for patients evaluated at least six months after achieving clinical cure and at least one year after completing terbinafine hydrochloride therapy, the clinical relapse rate was approximately 15%.

16 HOW SUPPLIED/STORAGE AND HANDLING

Terbinafine tablets USP, 250 mg are white, round, flat, beveled edged tablets embossed ‘250’ on one side and ‘RDY’ on other side and are supplied in bottles of 30, 90,100, 500 and unit dose packages of 100 (10 x 10).

Bottles of 30 NDC 55111-250-30

Bottles of 90 NDC 55111-250-90

Bottles of 100 NDC 55111-250-01

Bottles of 500 NDC 55111-250-05

Unit dose packages of 100 (10 x 10) NDC 55111-250-78

Store at 20°-25°C (68°-77°F) [see USP Controlled Room Temperature]; in a tight container. Protect from light.

17 PATIENT COUNSELING INFORMATION

[See FDA-Approved Patient Labeling (Patient Information)]

Patients taking terbinafine tablets should receive the following information and instructions:

- Patients should take one 250 mg tablet once daily for 6 weeks for treatment of fingernail onychomycosis or once daily for 12 weeks for treatment of toenail onychomycosis. The optimal clinical effect is seen some months after mycological cure and cessation of treatment due to the time period required for outgrowth of healthy nail.
- Patients should be advised to immediately report to their physician any symptoms of persistent nausea, anorexia, fatigue, vomiting, right upper abdominal pain, jaundice, dark urine or pale stools. Terbinafine tablets treatment should be discontinued.
- Patients should be advised to report to their physician any signs of taste disturbance, smell disturbance and/or depressive symptoms. Terbinafine tablets treatment should be discontinued.
- Patients should be advised to immediately report to their physician or get emergency help if they experience any of the following symptoms: hives, mouth sores, blistering and peeling of skin, swelling of face, lips, tongue, or throat, difficulty swallowing or breathing. Terbinafine tablets treatment should be discontinued.
- Patients should be advised to report to their physician any symptoms of new onset or worsening lupus erythematosus. Symptoms can include erythema, scaling, loss of pigment, and unusual photosensitivity that can result in a rash. Terbinafine hydrochloride treatment should be discontinued.
- Photosensitivity reactions have been reported with the use of Terbinafine hydrochloride. Patients should be advised to minimize exposure to natural and artificial sunlight (tanning beds or UVA/B treatment) while using Terbinafine hydrochloride.
- Measurement of serum transaminases (ALT and AST) is advised for all patients before taking terbinafine tablets.
- Patients should be advised that if they forget to take terbinafine tablets, to take their tablets as soon as they remember, unless it is less than four hours before the next dose is due. Patients should also be advised that if they take too many terbinafine tablets they should call their physician.

PATIENT PACKAGE INSERT SECTION

PATIENT INFORMATION

TERBINAFINE TABLETS USP

Read this Patient Information before you start taking terbinafine tablets and each time you get a refill. There may be new information. This information does not take the place of talking to your doctor about your medical condition or your treatment.

What are terbinafine tablets?

Terbinafine tablet is a prescription antifungal medicine used to treat fungal infections of the fingernails and toenails (onychomycosis).

Your doctor should do tests to check you for fungal infection of your nails before you start terbinafine tablets.

It is not known if terbinafine hydrochloride is safe and effective in children for the treatment of onychomycosis.

Who should not take terbinafine tablets?

Do not take terbinafine hydrochloride if you are allergic to terbinafine hydrochloride when taken by mouth.

What should I tell my doctor before taking terbinafine tablets?

Before you take terbinafine tablets, tell your doctor if you:

- have or had liver problems
- have a weakened immune system (immunocompromised)
- have lupus (an autoimmune disease)
- have kidney problems
- have any other medical conditions
- are pregnant or plan to become pregnant. It is not known if terbinafine tablets will harm your unborn baby. You should not start using terbinafine tablets during pregnancy without talking with your doctor.
- are breast-feeding or plan to breast-feed. Some terbinafine tablets passes into your milk and may harm your baby. Talk to your doctor about the best way to feed your baby if you take terbinafine tablets.

Tell your doctor about all the medicines you take, including prescription and nonprescription medicines, vitamins, and herbal supplements. Terbinafine tablets may affect the way other medicines work and other medicines may affect how terbinafine tablet works. Especially tell your doctor if you take:

- a medicine for depression
- a medicine for high blood pressure
- a medicine for heart problems
- desipramine (Norpramin)
- caffeine
- cyclosporine (Gengraf, Neoral, Sandimmune)
- fluconazole (Diflucan)
- rifampin (Rifater, Rifamate, Rimactane, Rifadine)
- cimetidine (Tagamet)

If you are not sure if your medicine is one listed above, ask your doctor or pharmacist.

Know the medicines you take. Keep a list of them to show your doctor and pharmacist when you get a new medicine.

How should I take terbinafine tablets?

- Take terbinafine tablets exactly as your doctor tells you to take it.
- Terbinafine tablets comes as a tablet that you take by mouth.
- Terbinafine tablets is usually taken:
- 1 time each day for 6 weeks to treat fungal infections of your fingernail, or
- 1 time each day for 12 weeks to treat fungal infections of your toenail
- You can take terbinafine tablets with or without food.
- If you forget to take terbinafine tablets, take your tablets as soon as you remember, unless it is less than 4 hours before your next dose is due. In this case, wait and take your next dose at the usual time.
- If you take too much terbinafine tablets call your doctor. You may have the following symptoms:
- nausea • vomiting
- stomach (abdominal) pain • dizziness
- rash • frequent urination
- headache

What are the possible side effects of terbinafine tablets?

Terbinafine tablets may cause serious side effects, including:

• liver problems that can lead to the need for liver transplant, or death. Tell your doctor right away if you get any of these symptoms of a liver problem:

- nausea • upper right stomach (abdominal) pain
- poor appetite • yellowing of your skin or eyes (jaundice)
- tiredness • dark (tea-colored) urine
- vomiting • pale or light colored stools

Your doctor should do a blood test to check you for liver problems before you take terbinafine tablets.

• change in taste or loss of taste may happen with terbinafine tablets. This usually improves within several weeks after stopping terbinafine tablets, but may last for a long time or may become permanent. Tell your doctor if you have:

- change in taste or loss of taste
- poor appetite
- unwanted weight loss, or
- change in mood or depressive symptoms

- change in smell or loss of smell may happen with terbinafine tablets. This may improve after stopping terbinafine tablets, but may last for a long time or may become permanent.

• depressive symptoms. Tell your doctor right away if you have any of these signs or symptoms:

- feel sad or worthless
- change in sleep pattern
- loss of energy or interest in daily activities
- restlessness
- mood changes

- serious skin or allergic reactions. Tell your doctor right away or get emergency help if you get any of these symptoms:

skin rash, hives, sores in your mouth, or your skin blisters and peels

swelling of your face, eyes, lips, tongue or throat, trouble swallowing or breathing

• new or worsening lupus (an autoimmune disease). Stop taking terbinafine tablets and tell your doctor if you experience any of the following:

- progressive skin rash that is scaly, red, shows scarring, or loss of pigment
- unusual sensitivity to the sun that can lead to a rash

The most common side effects of terbinafine tablets include: headache, diarrhea, rash, dyspepsia, liver enzyme abnormalities, pruritus, taste disturbance, nausea, abdominal pain, and flatulence.

Tell your doctor if you have any side effect that bothers you or that does not go away.

These are not all of the possible side effects of terbinafine tablets. For information, ask your doctor or pharmacist.

Call your doctor for medical advice about side effects.

You may report side effects to FDA at 1-800-FDA-1088.

How do I Store terbinafine tablets?

• Store terbinafine tablets at 20°-25°C (68°-77°F).

• Keep terbinafine tablets in a tightly closed container and away from light.

Keep terbinafine tablets and all medicines out of the reach of children.

General information about the safe and effective use of terbinafine tablets.

Medicines are sometimes prescribed for purposes other than those listed in Patient Information. Do not use terbinafine tablets for a condition for which it was not prescribed. Do not give terbinafine tablets to other people, even if they have the same symptoms that you have. It may harm them.

This Patient Information summarizes the most important information about terbinafine tablets. If you would like more information, talk with your doctor. You can ask your pharmacist or doctor for information about terbinafine tablets that is written for health professionals.

What are the ingredients in terbinafine tablets?

Active ingredient: terbinafine hydrochloride.

Inactive ingredients: colloidal silicon dioxide, croscarmellose sodium, hypromellose, magnesium stearate, microcrystalline cellulose. This Patient Information has been approved by the U.S. Food and Drug Administration.

To reorder additional patient information sheets, please contact Dr. Reddy’s Customer Service at 1-866-733-3952.

Rx Only

Manufactured by:

Dr. Reddy’s Laboratories Limited

Bachupally - 500 090 INDIA

Revised: 0812

PACKAGE LABEL.PRINCIPAL DISPLAY PANEL SECTION

Container label